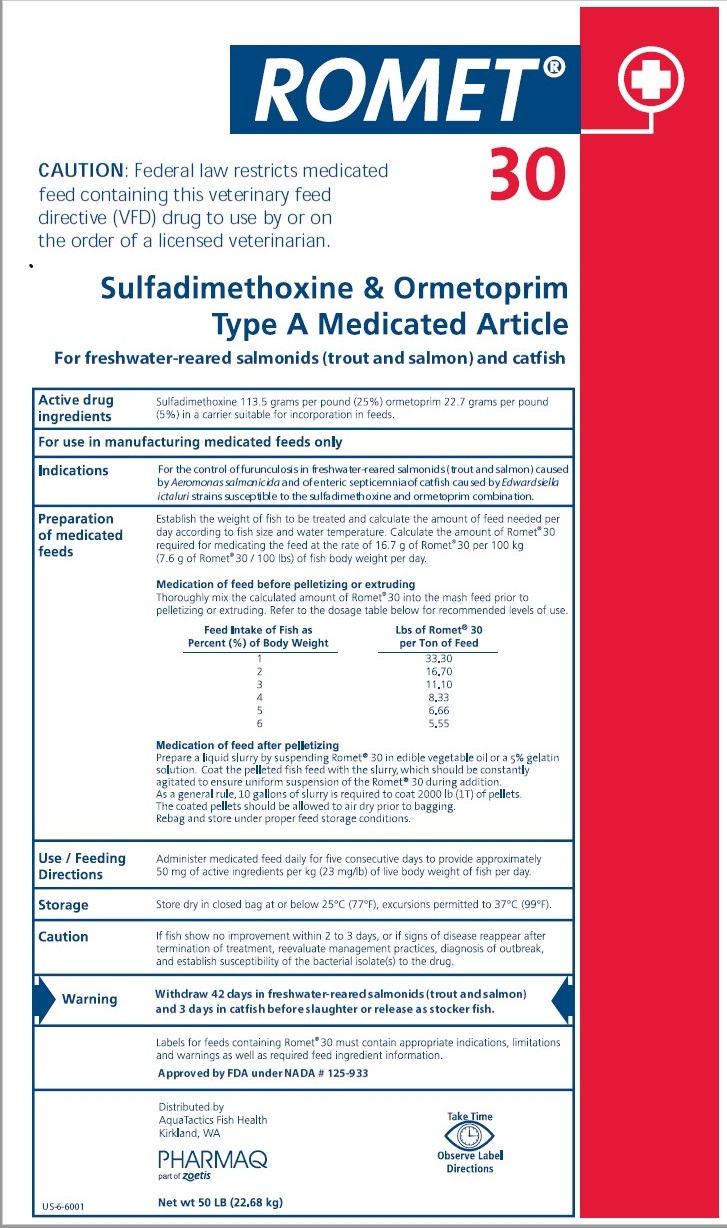 DRUG LABEL: ROMET
NDC: 15331-0103 | Form: Powder
Manufacturer: PHARMAQ AS
Category: animal | Type: VFD TYPE A MEDICATED ARTICLE ANIMAL DRUG LABEL
Date: 20230718

ACTIVE INGREDIENTS: Sulfadimethoxine 113.5 g/0.45 kg; Ormetoprim 22.7 g/0.45 kg

ROMET 30
Sulfadimethoxine & Ormetoprim
Type A Medicated Article
For freshwater-reared salmonids (trout and salmon) and catfish

CAUTION:

Federal law restricts medicated feed containing this veterinary feed directive (VFD) drug to use by or on the order of a licensed veterinarian

Active drug ingredients

Sulfadidemthoxine 113.5 grams per pound (25%) ormetoprim 22.7 grams per pound (5%) in a carrier suitable for incorporation in feeds.

Indications

For control of furunculosis in freshwater-reared salmonids (trout and salmon) caused by Aeromonas salmonicida and of enteric septicemia of catfish caused by Edwardsiella ictaluri strains susceptible to the sulfadimethoxine and ormetoprim combination.

Preparation of medicated feeds

Establish the weight of fish to be treated and calculate the amount of feed needed per day according to fish size and water temperature. Calculate the amount of Romet® 30 required for medicating the feed at the rate of 16.7 g of Romet®30 per 100 kg (7.6 g of Romet® 30/100 lbs) of fish body weight per day.

Medication of feed before pelletizing or extruding

Thoroughly mix the calculated amount of Romet® 30 into the mash feed prior to pelletizing or extruding. Refer to the dosage table below for recommended levels of use.

Feed Intake of Fish as; Percent (%) of Body Weight | Lbs of Romet® 30; per Ton of Feed
1 | 33.30
2 | 16.70
3 | 11.10
4 | 8.33
5 | 6.66
6 | 5.55

Medication of feed after pelletizing

Prepare a liquid slurry by suspending Romet® 30 in a 5% gelatin solution. Coat the pelleted fish feed with the slurry, which should be constantly agitated to ensure uniform suspension of the Romet® 30 during addition. As a general rule, 10 gallons of gelatin solution is required to coat 2000 lb (1T) of pellets. The coated pellets be allowed to dry prior to bagging. Do NOT top dress pellets with Romet® 30 in a vegetable or fish oil suspension.

Use/Feeding Directions

Administer medicated feed daily for five consecutive days to provide approximately 50 mg of active ingredients per kg (23 mg/lb) of live body of fish per day.

Storage

Store dry in closed bag at or below 25° C (77° F), excursions permitted to 37° C (99° F)

Caution

If fish show no improvement within 2 to 3 days, or if signs of disease reappear after termination of treatment, reevaluate management practices, diagnosis of outbreak and establish susceptibility of the bacterial isolate(s) to the drug.

Warning

Withdraw 42 days in freshwater-reared salmonids (trout and salmon) and 3 days in catfish before slaughter or release as stocker fish.

Labels for feeds containing Romet® 30 must contain appropriate indications, limitations and warnings as well as required feed ingredient information

Approved by FDA under NADA # 125-933

Marketed by

PHARMAQ

part of Zoetis

PHARMAQ AS

Skogmo Industriomrade

N-7863 Overhalla

Norway

US-4-6001 Net wt 50 LB (22.68 kg)

Take Time

Observe Label Directions

Made in USA